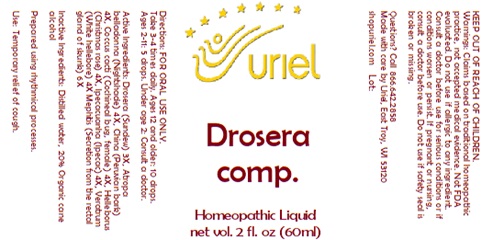 DRUG LABEL: Drosera comp.
NDC: 48951-4184 | Form: LIQUID
Manufacturer: Uriel Pharmacy Inc.
Category: homeopathic | Type: HUMAN OTC DRUG LABEL
Date: 20241119

ACTIVE INGREDIENTS: DROSERA ROTUNDIFOLIA 3 [hp_X]/1 mL; ATROPA BELLADONNA 4 [hp_X]/1 mL; QUILLAJA SAPONARIA BARK 4 [hp_X]/1 mL; PROTORTONIA CACTI 4 [hp_X]/1 mL; HELLEBORUS FOETIDUS ROOT 4 [hp_X]/1 mL; IPECAC 4 [hp_X]/1 mL; MEPHITIS MEPHITIS ANAL GLAND FLUID 6 [hp_X]/1 mL; VERATRUM ALBUM ROOT 4 [hp_X]/1 mL
INACTIVE INGREDIENTS: WATER; ALCOHOL

Drosera comp.

INDICATIONS AND USAGE

Directions: FOR ORAL USE ONLY.

DOSAGE AND ADMINISTRATION

Take 3-4 times daily. Ages 12 and older: 10 drops. Ages 2-11: 5 drops. Under age 2: Consult a doctor.

ACTIVE INGREDIENT

Active Ingredients: Drosera (Sundew) 3X, Atropa belladonna (Nightshade) 4X, China (Peruvian bark) 4X, Coccus cacti (Cochineal bug, female) 4X, Helleborus (Christmas rose) 4X, Ipecacuanha (Ipecac) 4X, Veratrum (White hellebore) 4X, Mephitis (Secretion from the rectal gland of skunk) 4X.

Inactive Ingredients: Distilled water, 20% Organic cane alcohol

Prepared using rhythmical processes

PURPOSE

Use: Temporary relief of cough.

KEEP OUT OF REACH OF CHILDREN.

WARNINGS

Warnings: Claims based on traditional homeopathic practice, not accepted medical evidence. Not FDA evaluated. Do not use if allergic to any ingredient. Consult a doctor before use for serious conditons or if conditons worsen or persist. If pregnant or nursing, consult a doctor before use. Do not use if safety seal is broken or missing.

QUESTIONS

Questions? Call 866.642.2858 Made with care by Uriel, East Troy, WI 53120 shopuriel.com Lot: